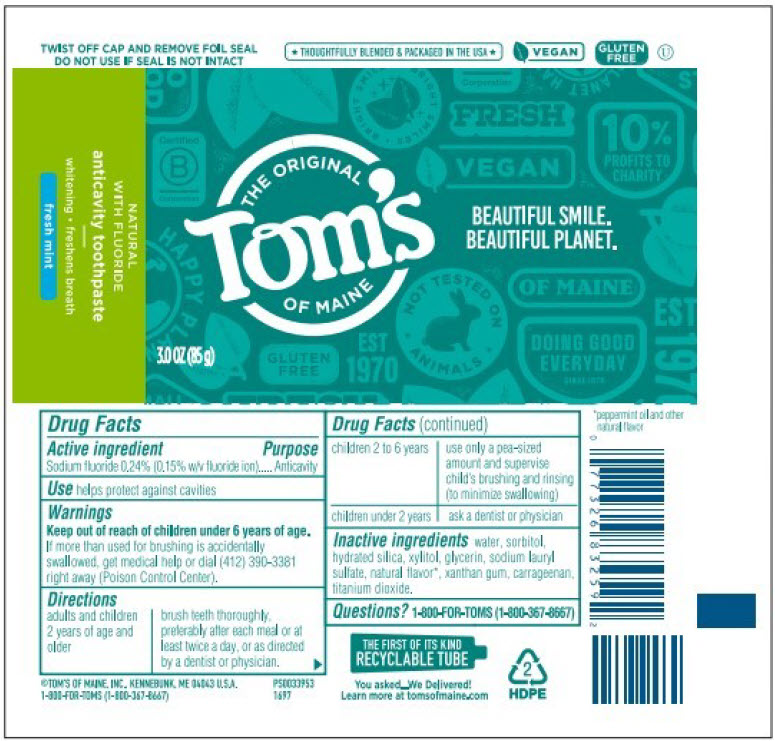 DRUG LABEL: Natural Fluoride Fresh Mint
NDC: 51009-238 | Form: PASTE, DENTIFRICE
Manufacturer: Tom's of Maine, Inc.
Category: otc | Type: HUMAN OTC DRUG LABEL
Date: 20260206

ACTIVE INGREDIENTS: SODIUM FLUORIDE 0.00243 g/1 g
INACTIVE INGREDIENTS: SORBITOL; WATER; HYDRATED SILICA; GLYCERIN; XYLITOL; SODIUM LAURYL SULFATE; PEPPERMINT OIL; XANTHAN GUM; TITANIUM DIOXIDE; CARRAGEENAN

Natural Fluoride Toothpaste, Fresh Mint
cavity protection / whitening / fresh breath

Drug Facts

Active ingredient

Sodium fluoride 0.24% (0.15% w/v fluoride ion)

Purpose

Anticavity

Use

helps protect against cavities

Warnings

Keep out of reach of children under 6 years of age. If more than used for brushing is accidentally swallowed, get medical help or dial (412) 390-3381 right away (Poison Control Center).

Directions

adults and children 2 years of age and older | brush teeth thoroughly, preferably after each meal or at least twice a day, or as directed by a dentist or physician.
children 2 to 6 years | use only a pea-sized amount and supervise child's brushing and rinsing (to minimize swallowing)
children under 2 years | ask a dentist or physician

Inactive ingredients

hydrated silica, water, sorbitol, glycerin, xylitol, sodium lauryl sulfate, natural flavor [Peppermint oil and other natural flavor] , xanthan gum, titanium dioxide, carrageenan.

Questions?

1-800-FOR-TOMS (1-800-367-8667) M - F 8:30 a.m. - 5 p.m. ET

PRINCIPAL DISPLAY PANEL - 85 g Tube Label

THE ORIGINAL
Tom's
OF MAINE

BEAUTIFUL SMILE.
BEAUTIFUL PLANET.

3.0 OZ (85 g)

NATURAL
WITH FLUORIDE
anticavity toothpaste
whitening ∙ freshens breath
fresh mint